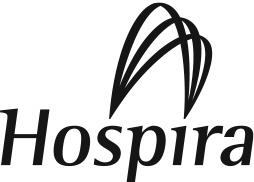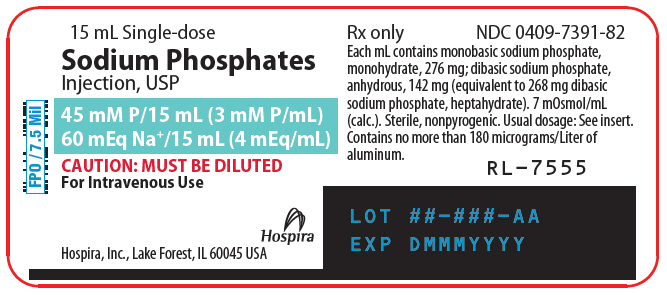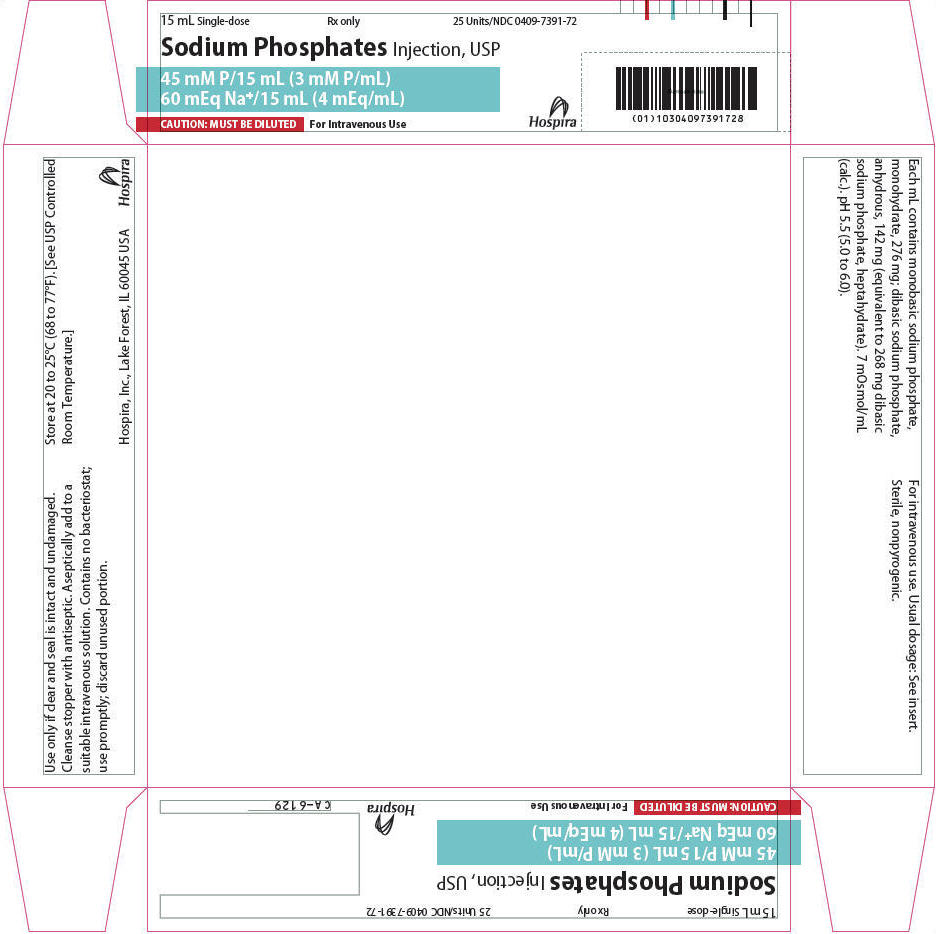 DRUG LABEL: Sodium Phosphates
NDC: 0409-7391 | Form: INJECTION, SOLUTION
Manufacturer: Hospira, Inc.
Category: prescription | Type: HUMAN PRESCRIPTION DRUG LABEL
Date: 20251013

ACTIVE INGREDIENTS: SODIUM PHOSPHATE, MONOBASIC, MONOHYDRATE 276 mg/1 mL; SODIUM PHOSPHATE, DIBASIC, ANHYDROUS 142 mg/1 mL
INACTIVE INGREDIENTS: WATER

SODIUM PHOSPHATES
Injection, USP

45 mM P in 15 mL

(3 mM P and 4 mEq Na^+/mL)

FOR ADDITIVE USE ONLY AFTER DILUTION IN I.V. FLUIDS

Plastic Vial

Rx only

DESCRIPTION

Sodium Phosphates Injection, USP, 3 mM P/mL (millimoles/mL), is a sterile, nonpyrogenic, concentrated solution containing a mixture of monobasic sodium phosphate and dibasic sodium phosphate in water for injection.

The solution is administered after dilution by the intravenous route as an electrolyte replenisher. It must not be administered undiluted.

Each mL contains 276 mg of monobasic sodium phosphate, monohydrate and 142 mg of dibasic sodium phosphate, anhydrous (equivalent to 268 mg of dibasic sodium phosphate, heptahydrate).

One mM of phosphorus weighs 31 mg, and the product provides 93 mg (approximately 3 mM) of phosphorus/mL plus 92 mg (4 mEq) of sodium/mL. Note: 1 mM P = 1 mM PO4. It contains no bacteriostat, antimicrobial agent or added buffer. The pH is 5.5 (5.0 to 6.0). The osmolar concentration is 7 mOsmol/mL (calc).

The solution is intended as an alternative to potassium phosphate to provide phosphorus for addition to large volume infusion fluids for intravenous use.

It is provided as a 15 mL partial fill single-dose vial; when lesser amounts are required, the unused portion should be discarded with the entire unit.

Monobasic Sodium Phosphate, USP (monohydrate) is chemically designated NaH2PO4 • H2O, white, odorless crystals or granules freely soluble in water.

Dibasic Sodium Phosphate, USP (anhydrous) is chemically designated Na2HPO4, colorless or white granular salt freely soluble in water.

The semi-rigid container is fabricated from a specially formulated polyolefin. It is a copolymer of ethylene and propylene. The safety of the plastic has been confirmed by tests in animals according to USP biological standards for plastic containers. The container requires no vapor barrier to maintain the proper drug concentration.

CLINICAL PHARMACOLOGY

Phosphorus in the form of organic and inorganic phosphate has a variety of important biochemical functions in the body and is involved in many significant metabolic and enzyme reactions in almost all organs and tissues. It exerts a modifying influence on the steady state of calcium levels, a buffering effect on acid-base equilibrium and a primary role in the renal excretion of hydrogen ion.

Phosphorus is present in plasma and other extracellular fluid, in cell membranes and intracellular fluid, as well as in collagen and bone tissues. Phosphorus in the extracellular fluid is primarily in inorganic form and plasma levels may vary somewhat with age. The ratio of disodium phosphate and monosodium phosphate in the extracellular fluid is 4 to 1 (80% to 20%) at the normal pH of 7.4. This buffer ratio varies with the pH, but owing to its relatively low concentration, it contributes little to the buffering capacity of the extracellular fluid.

Phosphorus, present in large amounts in erythrocytes and other tissue cells, plays a significant intracellular role in the synthesis of high energy organic phosphates. It has been shown to be essential to maintain red cell glucose utilization, lactate production, and the concentration of both erythrocyte adenosine triphosphate (ATP) and 2,3 diphosphoglycerate (DPG), and must be deemed as important to other tissue cells. Hypophosphatemia should be avoided during periods of total parenteral nutrition, or other lengthy periods of intravenous infusions. It has been suggested that patients receiving total parenteral nutrition receive 12 to 15 mM phosphorus per 250 g of dextrose. Serum phosphorus levels should be regularly monitored and appropriate amounts of phosphorus should be added to the infusions to maintain normal serum phosphorus levels. Intravenous infusion of inorganic phosphorus may be accompanied by a decrease in the serum level and urinary excretion of calcium. The normal level of serum phosphorus is 3.0 to 4.5 mg/100 mL in adults; 4.0 to 7.0 mg/100 mL in children.

Intravenously infused phosphorus not taken up by the tissues is excreted almost entirely in the urine. Plasma phosphorus is believed to be filterable by the renal glomeruli, and the major portion of filtered phosphorus (greater than 80%) is actively reabsorbed by the tubules. Many modifying influences tend to alter the amount excreted in the urine.

Sodium is the principal cation of extracellular fluid. It comprises more than 90% of the total cations at its normal plasma concentration of approximately 142 mEq/liter. While the sodium ion can diffuse across cell membranes, intracellular sodium is maintained at a much lower concentration than extracellular sodium through the expenditure of energy by the cell (so called "sodium cation pump"). Loss of intracellular potassium ion is usually accompanied by an increase in intracellular sodium ion.

When serum sodium concentration is low, the secretion of antidiuretic hormone (ADH) by the pituitary is inhibited, thereby preventing water reabsorption by the distal renal tubules. On the other hand, adrenal secretion of aldosterone increases renal tubular reabsorption of sodium in an effort to re-establish normal serum sodium concentration.

INDICATIONS AND USAGE

Sodium Phosphates Injection, USP, 3 mM P/mL is indicated as a source of phosphorus, for addition to large volume intravenous fluids, to prevent or correct hypophosphatemia in patients with restricted or no oral intake. It is also useful as an additive for preparing specific parenteral fluid formulas when the needs of the patient cannot be met by standard electrolyte or nutrient solutions.

The concomitant amount of sodium (Na^+ 4 mEq/mL) must be calculated into total electrolyte dose of such prepared solutions.

CONTRAINDICATIONS

Sodium phosphate is contraindicated in diseases where high phosphorus or low calcium levels may be encountered, and in patients with hypernatremia.

WARNINGS

Sodium Phosphates Injection, USP, 3 mM P/mL must be diluted and thoroughly mixed before use.

To avoid phosphorus intoxication, infuse solutions containing sodium phosphate slowly. Infusing high concentrations of phosphorus may result in a reduction of serum calcium and symptoms of hypocalcemic tetany. Calcium levels should be monitored.

Solutions containing sodium ions should be used with great care, if at all, in patients with congestive heart failure, severe renal insufficiency and in clinical states in which there exists edema with sodium retention.

In patients with diminished renal function, administration of solutions containing sodium ions may result in sodium retention.

WARNING: This product contains aluminum that may be toxic. Aluminum may reach toxic levels with prolonged parenteral administration if kidney function is impaired. Premature neonates are particularly at risk because their kidneys are immature, and they require large amounts of calcium and phosphate solutions, which contain aluminum.

Research indicates that patients with impaired kidney function, including premature neonates, who receive parenteral levels of aluminum at greater than 4 to 5 mcg/kg/day accumulate aluminum at levels associated with central nervous system and bone toxicity. Tissue loading may occur at even lower rates of administration.

PRECAUTIONS

Do not administer unless solution is clear and seal is intact. Discard unused portion.

Phosphorus replacement therapy with sodium phosphate should be guided primarily by the serum phosphorus level and the limits imposed by the accompanying sodium (Na^+) ion.

Use with caution in patients with renal impairment, cirrhosis, cardiac failure and other edematous or sodium-retaining states.

Caution must be exercised in the administration of parenteral fluids, especially those containing sodium ions, to patients receiving corticosteroids or corticotropin.

PREGNANCY

Pregnancy: Animal reproduction studies have not been conducted with sodium phosphate. It is also not known whether sodium phosphate can cause fetal harm when administered to a pregnant woman or can affect reproduction capacity. Sodium phosphate should be given to a pregnant woman only if clearly needed.

PEDIATRIC USE

Pediatric Use: The safety and effectiveness of sodium phosphate has been established in pediatric patients (neonates, infants, children and adolescents).

GERIATRIC USE

Geriatric Use: An evaluation of current literature revealed no clinical experience identifying differences in response between elderly and younger patients. In general, dose selection for an elderly patient should be cautious, usually starting at the low end of the dosing range, reflecting the greater frequency of decreased hepatic, renal, or cardiac function, and of concomitant disease or other drug therapy.

Sodium ions and phosphorus are known to be substantially excreted by the kidney, and the risk of toxic reactions to this drug may be greater in patients with impaired renal function. Because elderly patients are more likely to have decreased renal function, care should be taken in dose selection, and it may be useful to monitor renal function.

ADVERSE REACTIONS

Adverse reactions involve the possibility of phosphorus intoxication. Phosphorus intoxication results in a reduction of serum calcium and the symptoms are those of hypocalcemic tetany. See WARNINGS.

OVERDOSAGE

In the event of overdosage, discontinue infusions containing sodium phosphate immediately and institute corrective therapy to restore depressed serum calcium and to reduce elevated serum sodium levels. See WARNINGS, PRECAUTIONS and ADVERSE REACTIONS.

DOSAGE AND ADMINISTRATION

Sodium Phosphates Injection, USP, 3 mM P/mL is administered intravenously only after dilution and thorough mixing in a larger volume of fluid. The dose and rate of administration are dependent upon the individual needs of the patient. Serum sodium, phosphorus and calcium levels should be monitored as a guide to dosage. Using aseptic technique, all or part of the contents of one or more vials may be added to other intravenous fluids to provide any desired number of millimoles (mM) of phosphorus.

In patients on total parenteral nutrition, approximately 12 to 15 mM of phosphorus (equivalent to 372 to 465 mg elemental phosphorus) per liter bottle of TPN solution containing 250 g dextrose is usually adequate to maintain normal serum phosphorus, though larger amounts may be required in hypermetabolic states. The amount of sodium and phosphorus which accompanies the addition of sodium phosphate also should be kept in mind, and if necessary, serum sodium levels should be monitored.

The suggested dose of phosphorus for infants receiving TPN is 1.5 to 2 mM P/kg/day.

Parenteral drug products should be inspected visually for particulate matter and discoloration prior to administration, whenever solution and container permit. See PRECAUTIONS.

HOW SUPPLIED

Sodium Phosphates Injection, USP, 3 mM P/mL is supplied as per below.

Unit of Sale | Concentration | Unit of Use
NDC 0409-7391-72 Tray containing 25 vials | 45 mM (3 mM P/mL) containing 60 mEq Na^+ (4.0 mEq/mL) | NDC 0409-7391-82 15 mL Single-dose Plastic Vial

Each container is partially filled to provide air space needed for complete vacuum withdrawal of the contents into the I.V. container.

Store at 20 to 25°C (68 to 77°F). [See USP Controlled Room Temperature.]

Hospira, Inc., Lake Forest, IL 60045 USA

LAB-1044-3.0

Revised: 01/2018

PRINCIPAL DISPLAY PANEL - 15 mL Vial Label

15 mL Single-dose

Sodium Phosphates
Injection, USP

45 mM P/15 mL (3 mM P/mL)
60 mEq Na^+/15 mL (4 mEq/mL)

CAUTION: MUST BE DILUTED
For Intravenous Use

Hospira

Hospira, Inc., Lake Forest, IL 60045 USA

PRINCIPAL DISPLAY PANEL - 15 mL Vial Tray

15 mL Single-dose
Rx only
25 Units/NDC 0409-7391-72

Sodium Phosphates Injection, USP

45 mM P/15 mL (3 mM P/mL)
60 mEq Na^+/15 mL (4 mEq/mL)

CAUTION: MUST BE DILUTED
For Intravenous Use
Hospira